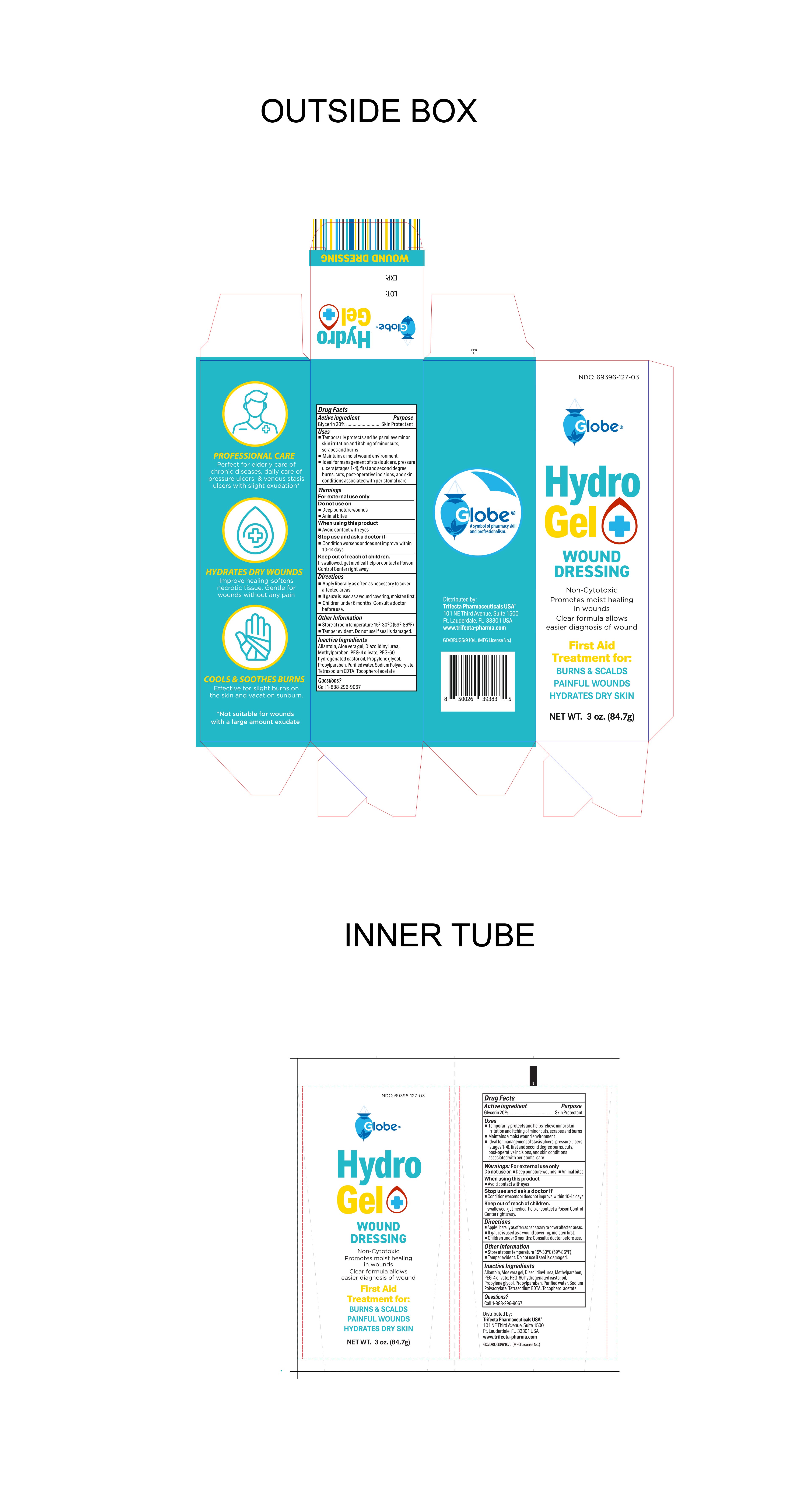 DRUG LABEL: Hydro Gel
NDC: 69396-127 | Form: GEL
Manufacturer: Trifecta Pharmaceuticals USA LLC
Category: otc | Type: HUMAN OTC DRUG LABEL
Date: 20240119

ACTIVE INGREDIENTS: GLYCERIN 20 g/100 g
INACTIVE INGREDIENTS: ALOE VERA LEAF; METHYLPARABEN; PEG-4 OLEATE; PROPYLENE GLYCOL; .ALPHA.-TOCOPHEROL ACETATE; ALLANTOIN; WATER; SODIUM POLYACRYLATE (2500000 MW); DIAZOLIDINYL UREA; PROPYLPARABEN; PEG-60 HYDROGENATED CASTOR OIL; EDETATE SODIUM

Globe Hydro Gel

Active Ingredient

Glycerin 20%

Purpose

Skin Protectant

Uses

- Temporarily protects and helps relieve minor skin irritation and itching of minor cuts, scrapes and burns
- Maintains a moist wound environment
- Ideal for managment of stasis ulcers, pressure ulcers (stages 1-4), first and second degree burns, cuts, post-operative incisions, and skin conditions associated with peristomal care.

Stop use and ask a doctor

- condition worsens or does not improve within 10-14 days

Keep out of the reach of children

If swallowed get medical help or contact Poison Control Center right away

When Using this product

Avoid contact with eyes

Directions

- Apply liberally as often as necessary to cover affected areas.
- If gauze is used as a wound covering, moisten first.
- Children under 6 months: Consult a doctor before use

Warning

For External Use Only

Do not use on Deep pumcture wounds or Animal Bites

Other information

Store at room temperature 15°-30°C (59°-86°F)

**Tamper evident. Do not use if seal is damaged

Inactive Ingredients

Allantoin, Aloe Vera gel, Diazolidinyl urea, Methylparaben, PEG-4 olivate, PEG-60, hydrogenated castor oil, Propylene glycol, Propylparaben, Purified water, Sodium Polyacrylate, Tetrasodium EDTA, Tocopherol acetate

Questions or Comments

Call Toll Free 1-888-296-9067

Distributed By

Trifecta Pharmaceuticals USA®

101 NE Third Avenue Suite 1500

Fort Lauderdale, FL. 33301 USA

www.trifecta-pharma.com